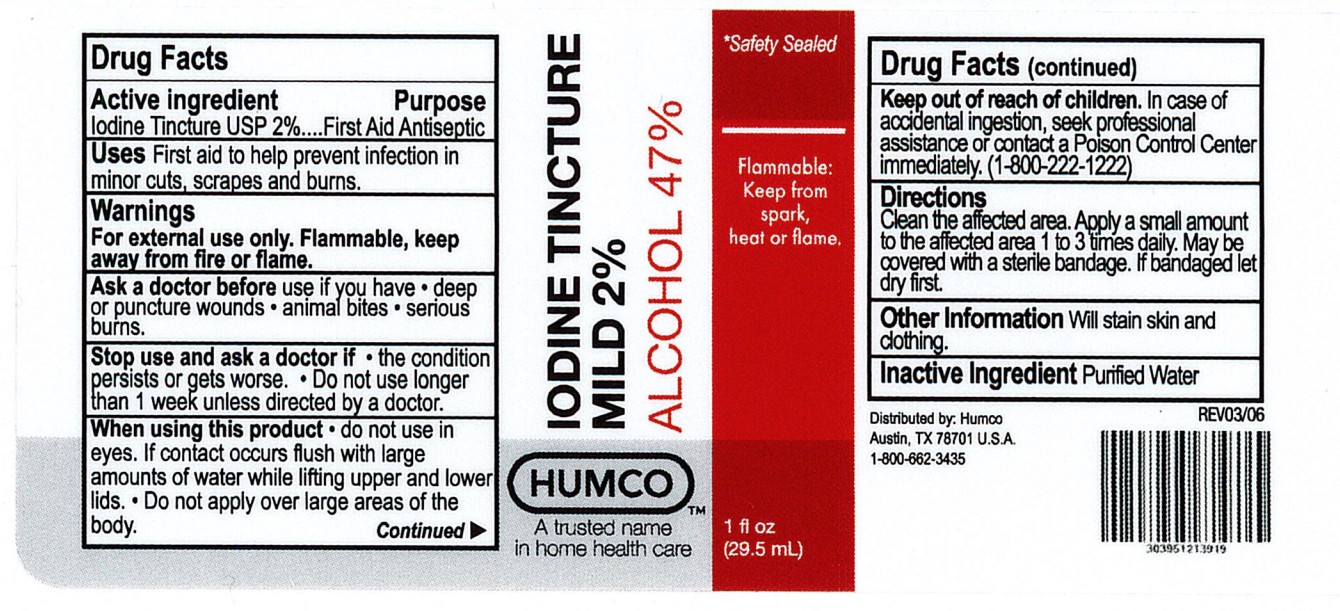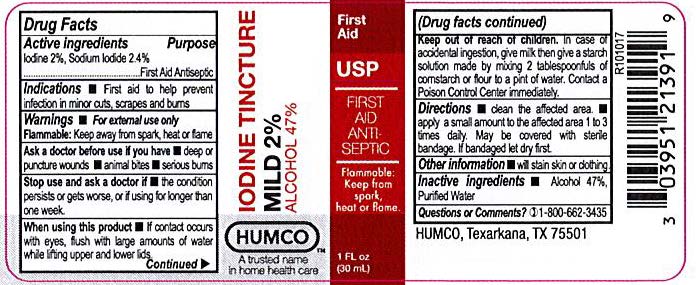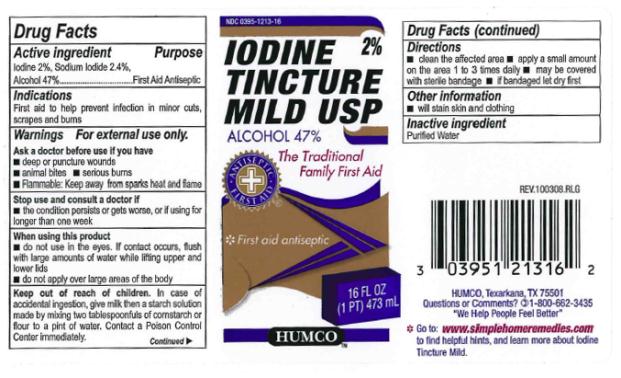 DRUG LABEL: Iodine Tincture Mild
NDC: 0395-1213 | Form: LIQUID
Manufacturer: Humco Holding Group, Inc.
Category: otc | Type: HUMAN OTC DRUG LABEL
Date: 20251203

ACTIVE INGREDIENTS: IODINE 20 mg/1 mL; SODIUM IODIDE 20.4 mg/1 mL; ALCOHOL 470 mg/1 mL
INACTIVE INGREDIENTS: WATER

Humco Iodine Ticture Mild, USP

Drug Facts

Active ingredient

Iodine 2%

Purpose

First Aid Antiseptic

Active ingredient

Sodium Iodide 2.4%

Purpose

First Aid Antiseptic

Active ingredient

Alcohol 47%

Purpose

First Aid Antiseptic

Indications

First aid to help prevent infection in minor cuts, scrapes and burns

Warnings

For external use only.

Ask a doctor before use if you have

- deep or puncture wounds
- animal bites
- serious burns
- Flammable: Keep away from sparks heat and flame

Stop use and consult doctor if

- the condition persists or gets worse, or if using for longer than one week

When using this product

- do not use in the eyes. If contact occurs, flush with large amounts of water while lifting upper and lower lids
- do not apply over large areas of the body

Keep out of reach of children.

In case of accidental ingestion, give milk then a starch solution made by mixing two tablespoonfuls of cornstarch or flour to a pint of water. Contact a Poison Control Center immediately.

Directions

- clean the affected area
- apply a small amount on the area 1 to 3 times daily
- may be covered with sterile bandage
- if bandaged let dry first

Other information

- will stain skin and clothing

Inactive ingredient

Purified Water